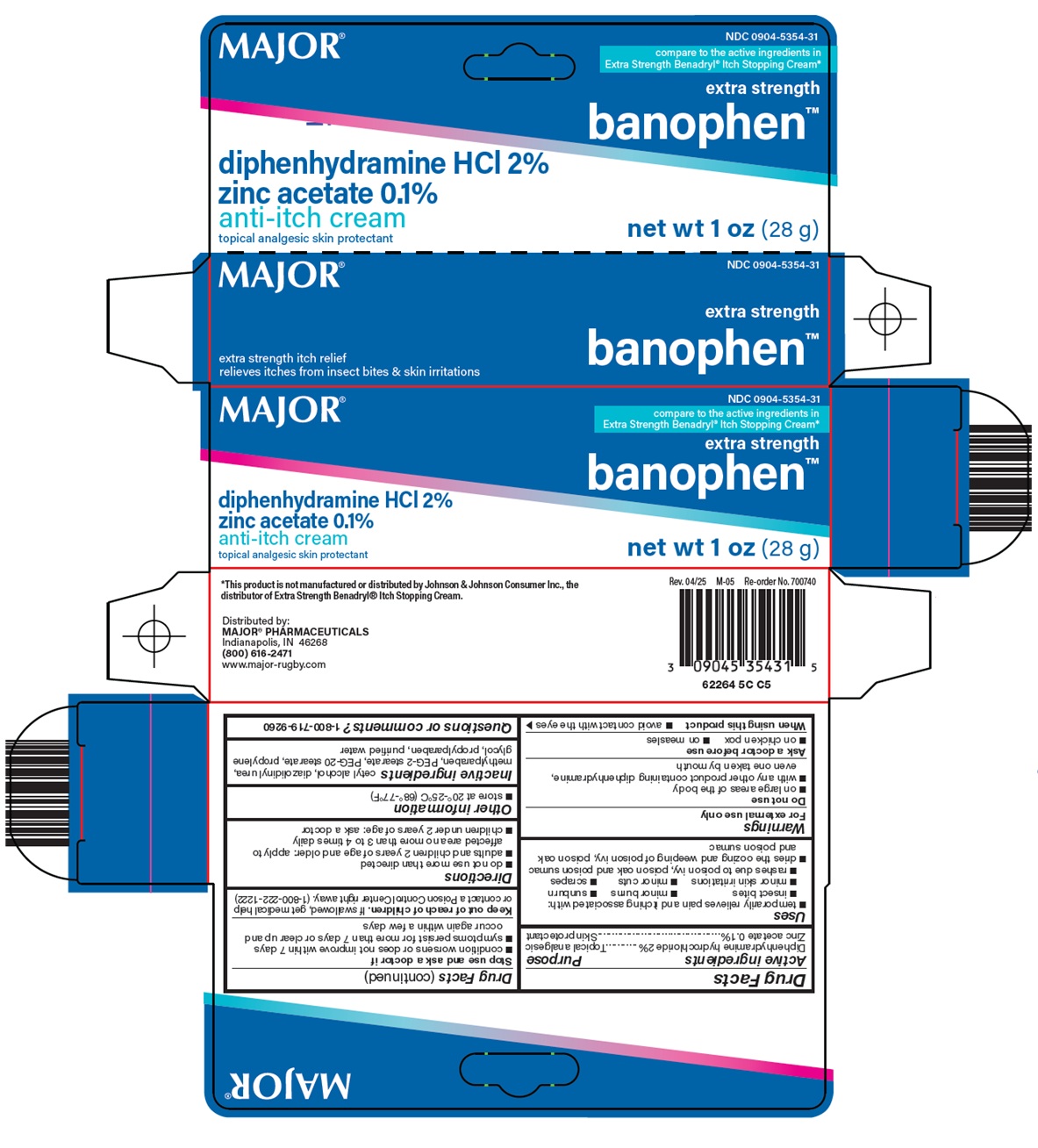 DRUG LABEL: Banophen
NDC: 0904-5354 | Form: CREAM
Manufacturer: Major Pharmaceuticals
Category: otc | Type: HUMAN OTC DRUG LABEL
Date: 20260213

ACTIVE INGREDIENTS: DIPHENHYDRAMINE HYDROCHLORIDE 2 g/100 g; ZINC ACETATE 0.1 g/100 g
INACTIVE INGREDIENTS: CETYL ALCOHOL; DIAZOLIDINYL UREA; METHYLPARABEN; DIETHYLENE GLYCOL MONO- AND DIPALMITOSTEARATE; PEG-20 STEARATE; PROPYLENE GLYCOL; PROPYLPARABEN; WATER

Major Pharmaceuticals Banophen™ Drug Facts

Active ingredients

Diphenhydramine hydrochloride 2%

Zinc acetate 0.1%

Purpose

Topical analgesic

Skin protectant

Uses

1. temporarily relieves pain and itching associated with:
  1. insect bites
  2. minor burns
  3. sunburn
  4. minor skin irritations
  5. minor cuts
  6. scrapes
  7. rashes due to poison ivy, poison oak and poison sumac
2. dries the oozing and weeping of poison ivy, poison oak and poison sumac

Warnings

For external use only

Do not use

1. on large areas of the body
2. with any other product containing diphenhydramine, even one taken by mouth

Ask a doctor before use

1. on chicken pox
2. on measles

When using this product

1. avoid contact with the eyes

Stop use and ask a doctor if

1. condition worsens or does not improve within 7 days
2. symptoms persist for more than 7 days or clear up and occur again within a few days

Keep out of reach of children.

If swallowed, get medical help or contact a Poison Control Center right away. (1-800-222-1222)

Directions

1. do not use more than directed
2. adults and children 2 years of age and older: apply to affected area no more than 3 to 4 times daily
3. children under 2 years of age: ask a doctor

Other information

1. store at 20°-25°C (68°-77°F)

Inactive ingredients

cetyl alcohol, diazolidinyl urea, methylparaben, PEG-2 stearate, PEG-20 stearate, propylene glycol, propylparaben, purified water

Questions or comments?

1-800-719-9260

Principal Display Panel

MAJOR®

compare to the active ingredients in Extra Strength Benadryl® Itch Stopping Cream

extra strength

banophen™

diphenhydramine HCl 2%

zinc acetate 0.1%

anti-itch cream

topical analgesic skin protectant

net wt 1 oz (28 g)